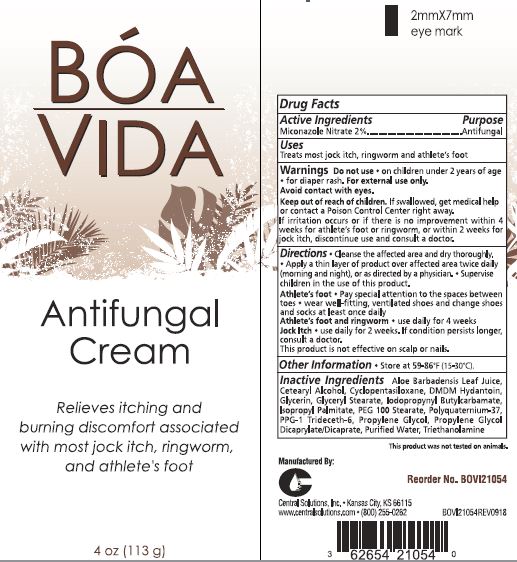 DRUG LABEL: BOA VIDA Antifungal
NDC: 62654-147 | Form: CREAM
Manufacturer: Central Solutions Inc
Category: otc | Type: HUMAN OTC DRUG LABEL
Date: 20241209

ACTIVE INGREDIENTS: MICONAZOLE NITRATE 2 g/100 g
INACTIVE INGREDIENTS: ALOE VERA LEAF; CETOSTEARYL ALCOHOL; CYCLOMETHICONE 5; DMDM HYDANTOIN; IODOPROPYNYL BUTYLCARBAMATE; GLYCERIN; GLYCERYL MONOSTEARATE; PEG-100 STEARATE; ISOPROPYL PALMITATE; POLYQUATERNIUM-37 (10000 MPA.S); PROPYLENE GLYCOL DICAPRYLATE; PROPYLENE GLYCOL DICAPRYLATE/DICAPRATE; PPG-1 TRIDECETH-6; PROPYLENE GLYCOL; WATER; TROLAMINE

Drug Facts 62654-147

Active Ingredients

Miconazole Nitrate 2%

Purpose

Skin protectant

Uses

Treats most jock itch, ringworm and athlete's foot

Warnings

For external use only.

Do not use on children under 2 years of age for diaper rash.

Keep out of reach of children.

If swallowed, get medical help or contact a Poison Control Center right away.

STOP USE

If irritation occurs or if there is no improvement withing 4 weeks for athlete's foot or ringworm, or within 2 weeks for jock itch, discontinue use and consult a doctor.

Directions

Cleanse the affected area and dry thoroughly.

Apply a thin layer of product over affected area twice daily (morning and night), or as directed by a physician. Supervise children in the use of this product.

Athlete's foot

Pay special attention to the spaces between toes

wear well-fitting, ventilated shoes and change shoes and socks at least once daily

Athlete's foot and ringworm

use daily for 4 weeks

Jock Itch

use daily for 2 weeks. If condition persists longer, consult a doctor.

This product is not effective on scalp or nails.

Other Information

Store at 59-86 F (15-30 C)

Inactive Ingredients

Aloe Barbadensis Leaf Juice, Cetearyl Alcohol, Cyclopentasiloxane, DMDM Hydantoin, Iodopropynyl Butylcarbamate, Glycerin, Glyceryl Stearate, PEG 100 Stearate, Isopropyl Palmitate, Polyquaternium-37, Propylene Glycol Dicaprylate Dicaprate, PPG-1 Trideceth-6, Propylene Glycol, Purified Water, Triethanolamine

PACKAGE LABEL

BOA

VIDA

Antifungal

Cream

Relieves itching and

burning discomfort associated

with most jock itch, ringworm,

and athlete's foot

4 oz. (113g)